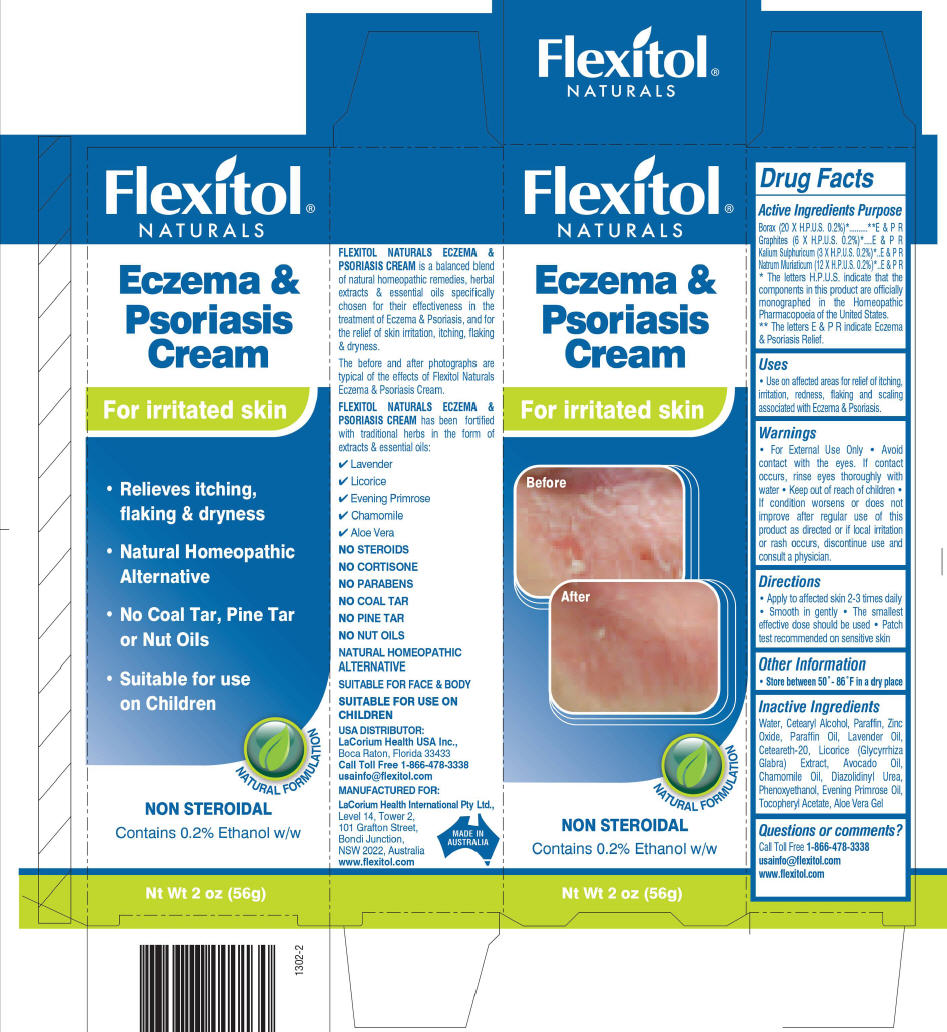 DRUG LABEL: Flexitol Naturals Eczema and Psoriasis
NDC: 43251-2231 | Form: CREAM
Manufacturer: LaCorium Health International Pty Ltd
Category: homeopathic | Type: HUMAN OTC DRUG LABEL
Date: 20120120

ACTIVE INGREDIENTS: Sodium Borate 20 [hp_X]/1 g; Graphite 6 [hp_X]/1 g; Potassium Sulfate 3 [hp_X]/1 g; Sodium Chloride 12 [hp_X]/1 g
INACTIVE INGREDIENTS: Zinc Oxide; Cetostearyl Alcohol; Lavandula Angustifolia Flower; Cocoa Butter; Glycyrrhiza Glabra; Avocado Oil; Shea Butter; Cetearyl Glucoside; Caprylyl Glycol; Sorbic Acid; Phenoxyethanol; Chamaemelum Nobile Flower Oil; Evening Primrose Oil; Water

Flexitol
NATURALS ®
ECZEMA
& PSORIASIS
CREAM

Drug Facts

ACTIVE INGREDIENT

Active ingredients | Purpose
Borax (20 X H.P.U.S. 0.2%) [The letters H.P.U.S. indicate that the components in this product are officially monographed in the Homeopathic Pharmacopoeia of the United States.] | [The letters E & P R indicate Eczema & Psoriasis Relief.] E & P R
Graphites (6 X H.P.U.S. 0.2%) | E & P R
Kalium Sulphuricum (3 X H.P.U.S. 0.2%) | E & P R
Natrum Muriaticum (12 X H.P.U.S. 0.2%) | E & P R

Uses

- Use on affected areas for relief of itching, irritation, redness, flaking and scaling associated with Eczema & Psoriasis.

Warnings

- For External Use Only
- Avoid contact with the eyes. If contact occurs, rinse eyes thoroughly with water

- Keep out of reach of children

STOP USE

- If condition worsens or does not improve after regular use of this product as directed or if local irritation or rash occurs, discontinue use and consult a physician.

Directions

- Apply to affected skin 2-3 times daily
- Smooth in gently
- The smallest effective dose should be used
- Patch test recommended on sensitive skin
- For best results use together with FLEXITOL NATURALS Eczema & Psoriasis Wash.

Other information

- Store between 50°- 86°F in a dry place

Inactive ingredients

Water, Cetearyl Alcohol, Paraffin, Zinc Oxide, Paraffin Oil, Lavender Oil, Ceteareth-20, Licorice (Glycyrrhiza Glabra) Extract, Avocado Oil, Chamomile Oil, Diazolidinyl Urea, Phenoxyethanol, Evening Primrose Oil, Tocopheryl Acetate, Aloe Vera Gel

Questions or comments?

Call Toll Free 1-866-478-3338
usainfo@flexitol.com
www.flexitol.com

PRINCIPAL DISPLAY PANEL - 56 g Carton

NON
STEROIDAL

Flexitol
NATURALS ®

Trust Flexitol . . .

ECZEMA
& PSORIASIS
CREAM

. . . it really works!

Before
After

For the Relief of
Skin Irritation, Itching,
Flaking & Dryness

Contains 0.2% Ethanol w/w

Net Wt 2 oz (56 g)